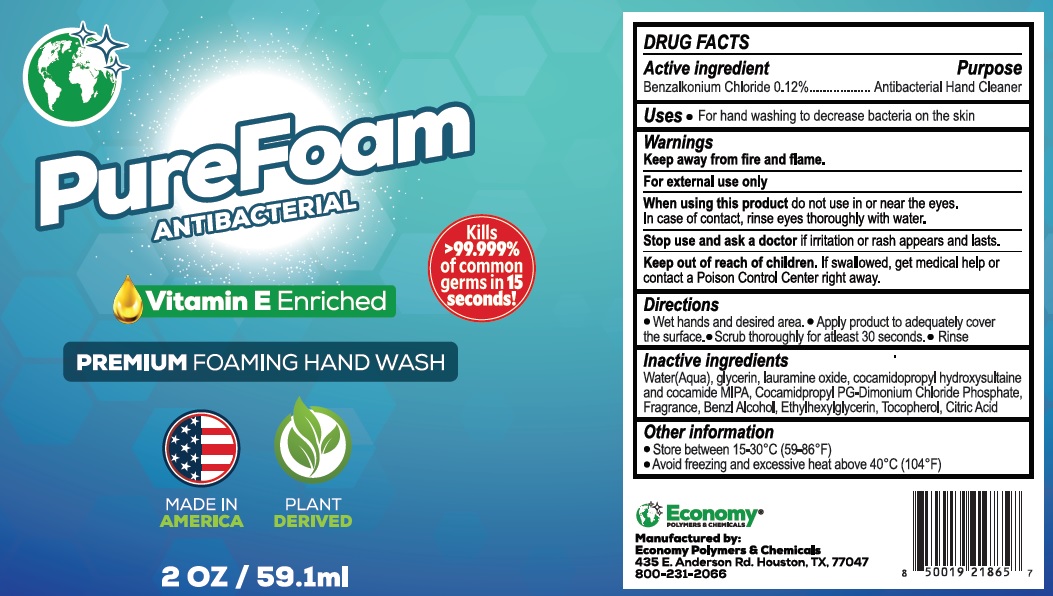 DRUG LABEL: PureFoam Antibacterial Hand Wash
NDC: 74830-547 | Form: LIQUID
Manufacturer: Economy Polymers and Chemicals
Category: otc | Type: HUMAN OTC DRUG LABEL
Date: 20201125

ACTIVE INGREDIENTS: BENZALKONIUM CHLORIDE 1.2 mg/1 mL
INACTIVE INGREDIENTS: WATER; GLYCERIN; LAURAMINE OXIDE; COCAMIDOPROPYL HYDROXYSULTAINE; COCAMIDE; COCAMIDOPROPYL PROPYLENE GLYCOL-DIMONIUM CHLORIDE PHOSPHATE; BENZYL ALCOHOL; ETHYLHEXYLGLYCERIN; TOCOPHEROL; CITRIC ACID MONOHYDRATE

PureFoam Antibacterial Hand Wash

Active ingredient

Benzalkonium Chloride 0.12%

Purpose

Antibacterial Hand Cleaner

Uses

- For hand washing to decrease bacteria on the skin

Warnings

Keep away from fire and flame.

For external use only

When using this product

do not use in or near the eyes. In case of contact, rinse eyes thoroughly with water.

Stop use and ask a doctor

if irritation or rash appears and lasts.

Keep out of reach of children.

If swallowed, get medical help or contact Poison Control Center right away.

DIRECTIONS

• Wet hands and desired area.
• Apply product to adequately cover the surface.
• Scrub thoroughly for atleast 30 seconds.
• Rinse

Inactive ingredients

Water (Aqua), glycerin, lauramine oxide, cocamidopropyl hydroxysultaine and cocamide MIPA, cocamidpropyl PG-Dimonium Chloride Phosphate, Fragrance, Benzl Alcohol, Ethylhexylglycerin, Tocopherol, Citric Acid

OTHER INFORMATION

• Store between (15-20C (59-86F)
• Avoid freezing and excessive heat above 40C (104F)